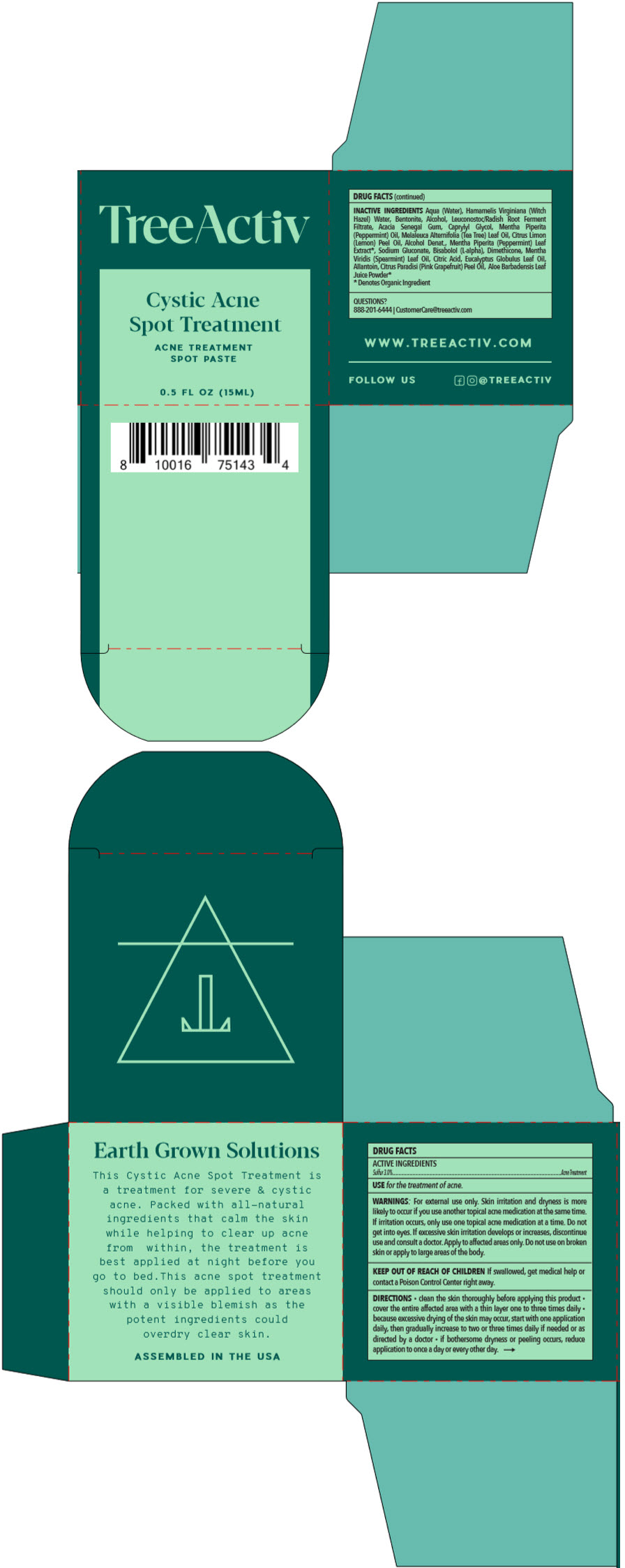 DRUG LABEL: TreeActiv Cystic Acne Spot Treatment
NDC: 72841-201 | Form: PASTE
Manufacturer: Leiluna LLC
Category: otc | Type: HUMAN OTC DRUG LABEL
Date: 20250408

ACTIVE INGREDIENTS: SULFUR 30 mg/1 mL
INACTIVE INGREDIENTS: WATER; HAMAMELIS VIRGINIANA TOP WATER; BENTONITE; ALCOHOL; LEUCONOSTOC/RADISH ROOT FERMENT FILTRATE; ACACIA; CAPRYLYL GLYCOL; PEPPERMINT OIL; TEA TREE OIL; LEMON OIL, COLD PRESSED; MENTHA PIPERITA LEAF; LEVOMENOL; SODIUM GLUCONATE; DIMETHICONE, UNSPECIFIED; SPEARMINT OIL; CITRIC ACID MONOHYDRATE; EUCALYPTUS OIL; ALLANTOIN; GRAPEFRUIT OIL; ALOE VERA LEAF

TreeActiv Cystic Acne Spot Treatment

DRUG FACTS

ACTIVE INGREDIENTS

Sulfur 3.0%

PURPOSE

Acne Treatment

USE

for the treatment of acne.

WARNINGS

For external use only. Skin irritation and dryness is more likely to occur if you use another topical acne medication at the same time. If irritation occurs, only use one topical acne medication at a time. Do not get into eyes. If excessive skin irritation develops or increases, discontinue use and consult a doctor. Apply to affected areas only. Do not use on broken skin or apply to large areas of the body.

KEEP OUT OF REACH OF CHILDREN

If swallowed, get medical help or contact a Poison Control Center right away.

DIRECTIONS

- clean the skin thoroughly before applying this product
- cover the entire affected area with a thin layer one to three times daily
- because excessive drying of the skin may occur, start with one application daily, then gradually increase to two or three times daily if needed or as directed by a doctor
- if bothersome dryness or peeling occurs, reduce application to once a day or every other day.

INACTIVE INGREDIENTS

Aqua (Water), Hamamelis Virginiana (Witch Hazel) Water, Bentonite, Alcohol, Leuconostoc/Radish Root Ferment Filtrate, Acacia Senegal Gum, Caprylyl Glycol, Mentha Piperita (Peppermint) Oil, Melaleuca Alternifolia (Tea Tree) Leaf Oil, Citrus Limon (Lemon) Peel Oil, Alcohol Denat., Mentha Piperita (Peppermint) Leaf Extract [Denotes Organic Ingredient] , Sodium Gluconate, Bisabolol (L-alpha), Dimethicone, Mentha Viridis (Spearmint) Leaf Oil, Citric Acid, Eucalyptus Globulus Leaf Oil, Allantoin, Citrus Paradisi (Pink Grapefruit) Peel Oil, Aloe Barbadensis Leaf Juice Powder

QUESTIONS?

888-201-6444 | CustomerCare@treeactiv.com

PRINCIPAL DISPLAY PANEL - 15 ML Jar Box

TreeActiv

Cystic Acne
Spot Treatment

ACNE TREATMENT
SPOT PASTE

0.5 FL OZ (15ML)